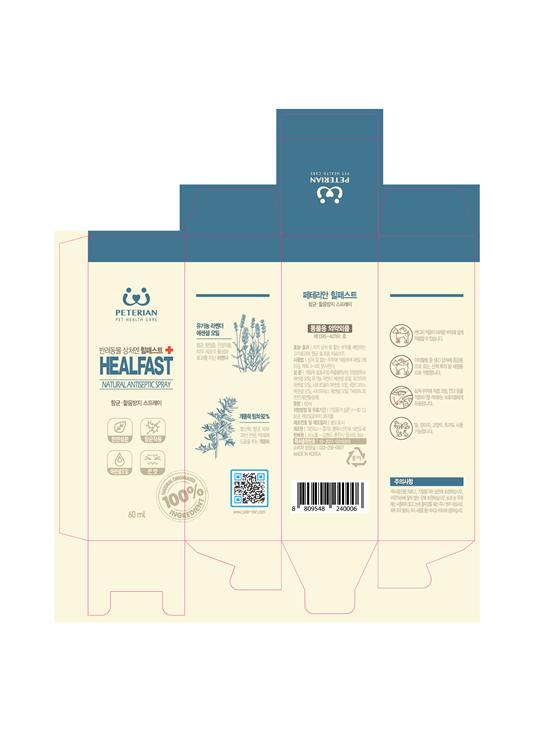 DRUG LABEL: Healfast
NDC: 78078-0001 | Form: LIQUID
Manufacturer: Peterian
Category: animal | Type: OTC ANIMAL DRUG LABEL
Date: 20200727

ACTIVE INGREDIENTS: WORMWOOD 55.8 g/60 mL
INACTIVE INGREDIENTS: water; ALCOHOL; Polysorbate 20; EUCALYPTUS OIL; Lavender oil; WEST INDIAN LEMONGRASS OIL; Rosemary oil

ACTIVE INGREDIENT

Artemisia extract (wormwood)

PURPOSE

Auxiliary and antibacterial effect to aid treatment

INDICATIONS AND USAGE

Suggested use: Apply this product to wounds and swollen areas, spraying 2 or more times daily, 3-4 times each time.

WARNINGS AND PRECAUTIONS

Avoid direct sunlight, and keep it in airtight container and room temperature.
Keep out of reach of children.
Do not use around eyes and around eyes, wash immediately if it gets into your eyes.
In case of skin irritation, discontinue use immediately and consult a veterinarian.